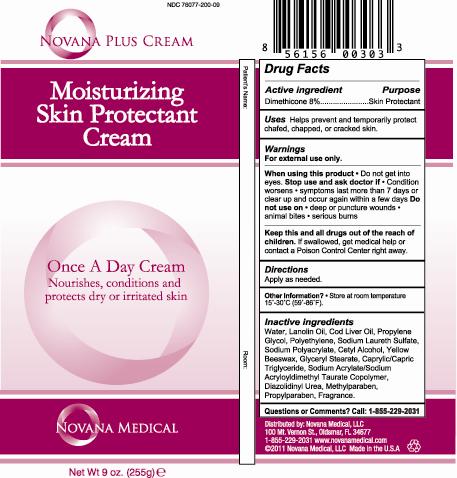 DRUG LABEL: Novana Moisturizing
NDC: 76077-200 | Form: CREAM
Manufacturer: NOVANA MEDICAL LLC
Category: otc | Type: HUMAN OTC DRUG LABEL
Date: 20120404

ACTIVE INGREDIENTS: Dimethicone .02 mL/1 mL
INACTIVE INGREDIENTS: Water; Lanolin; Cod Liver Oil; Propylene Glycol; HIGH DENSITY POLYETHYLENE; SODIUM POLYACRYLATE (2500000 MW); Cetyl Alcohol; YELLOW WAX; Glyceryl Monostearate; MEDIUM-CHAIN TRIGLYCERIDES; SODIUM ACRYLATE/SODIUM ACRYLOYLDIMETHYLTAURATE COPOLYMER (4000000 MW); Sodium Laureth Sulfate; Diazolidinyl Urea; Methylparaben; Propylparaben

Drug Facts

Active ingredient Purpose
Dimethicone 2%...................Skin Protectant

PURPOSE

Uses Helps to prevent and temporarily protect chafed, chapped, or cracked skin.

Warnings
When using this product • Do not get into eyes. Stop use and ask doctor if: • Condition worsens • Symptoms last more than 7 days or clear up and occur again within a few days. Do not use on: Deep or puncture wounds • Animal bites • Serious burns.

DOSAGE AND ADMINISTRATION

For external use only.

Inactive ingredients
Water, Lanolin Oil, Cod Liver Oil, Propylene Glycol, Polyethylene, Sodium Polyacrylate, Cetyl Alcohol, Beeswax, Glyceryl Stearate, Caprylic/Capric Triglyceride, Sodium Acrylate/Sodium AcryloyldimethylTaurate Copolymer, Sodium Laureth Sulfate, Diazolidinyl Urea, Methylparaben, Propylparaben, Fragrance.

KEEP OUT OF REACH OF CHILDREN

Keep this and all drugs out of the reach of children. If swallowed, get medical help or contact a Poison Control Center right away.

Directions
Apply as needed.